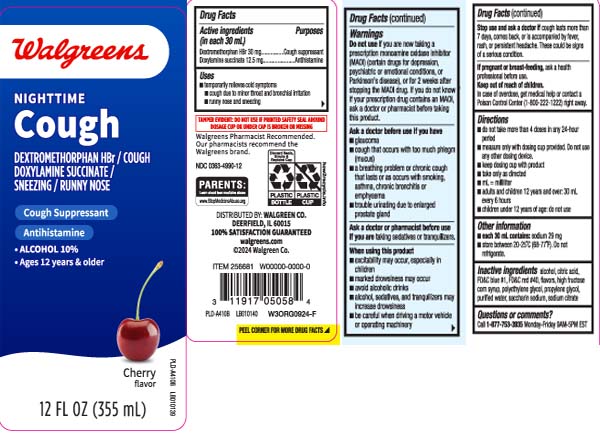 DRUG LABEL: Nighttime Cough
NDC: 0363-4990 | Form: LIQUID
Manufacturer: Walgreens
Category: otc | Type: HUMAN OTC DRUG LABEL
Date: 20251216

ACTIVE INGREDIENTS: DEXTROMETHORPHAN HYDROBROMIDE 30 mg/30 mL; DOXYLAMINE SUCCINATE 12.5 mg/30 mL
INACTIVE INGREDIENTS: PROPYLENE GLYCOL; WATER; ALCOHOL; ANHYDROUS CITRIC ACID; HIGH FRUCTOSE CORN SYRUP; POLYETHYLENE GLYCOL, UNSPECIFIED; SACCHARIN SODIUM; TRISODIUM CITRATE DIHYDRATE; FD&C BLUE NO. 1; FD&C RED NO. 40

Drug Facts

Active ingredients (in each 30 mL)

Dextromethorphan HBr 30 mg

Doxylamine succinate 12.5 mg

Purposes

Cough suppressant

Antihistamine

Uses

- temporarily relieves cold symptoms
  - cough due to minor throat and bronchial irritation
  - runny nose and sneezing

Warnings

Do not use

- if you are now taking a prescription monoamine oxidase inhibitor (MAOI) (certain drugs for depression, psychiatric or emotional conditions, or Parkinson’s disease), or for 2 weeks after stopping the MAOI drug. If you do not know if your prescription drug contains an MAOI, ask a doctor or pharmacist before taking this product.

Ask a doctor before use if you have

- glaucoma
- cough that occurs with too much phlegm (mucus)
- a breathing problem or chronic cough that lasts or as occurs with smoking, asthma, chronic bronchits, or emphysema
- trouble urinating due to enlarged prostate gland

Ask a doctor or pharmacist before use if you are taking

- sedatives or tranquilizers

When using this product

- excitability may occur, especially in children
- marked drowsiness may occur
- avoid alcoholic drinks
- be careful when driving a motor vehicle or operating machinery
- alcohol, sedatives and tranquilizers may increase drowsiness

Stop use and ask a doctor if

- cough lasts more than 7 days, comes back, or is accompanied by fever, rash, or persistent headache.

These could be signs of a serious condition.

If pregnant or breast-feeding,

ask a health professional before use.

Keep out of reach of children.

In case of overdose, get medical help or contact a Poison Control Center (1-800-222-1222) right away.

Directions

- do not take more than 4 doses in any 24-hour period
- measure only with dosing cup provided. Do not use any other dosing device.
- mL= milliliter
- keep dosing cup with product
- take only as directed
- adults and children 12 years and over: 30 mL every 6 hours
- children under 12 years of age: do not use

Other information

- each 30 mL contains: sodium 29 mg
- store between 20-25ºC (68-77ºF). Do not refrigerate.

Inactive ingredients

alcohol, citric acid, FD&C blue #1, FD&C red #40, flavor,high fructose corn syrup, polyethylene glycol, propylene glycol, purified water, saccharin sodium, sodium citrate

Questions or comments?

Call 1-877-753-3935 Monday-Friday 9AM-5PM EST

Principal Display Panel

NIGHTTIME

COUGH

DEXTROMETHORPHAN HBr / COUGH

DOXYLAMINE SUCCINATE /

SNEEZING / RUNNY NOSE

Cough Suppressant

Antihistamine

- ALCOHOL 10%
- Ages 12 years & older

Cherry flavor

FL OZ (mL)

TAMPER EVIDENT: DO NOT USE IF PRINTED SAFETY SEAL AROUND DOSAGE CUP OR UNDER CAP IS BROKEN OR MISSING

DISTRIBUTED BY WALGREENS CO.

DEERFIELD, IL 60016

Product Label

WALGREENS Nighttime Cough Cherry Flavor